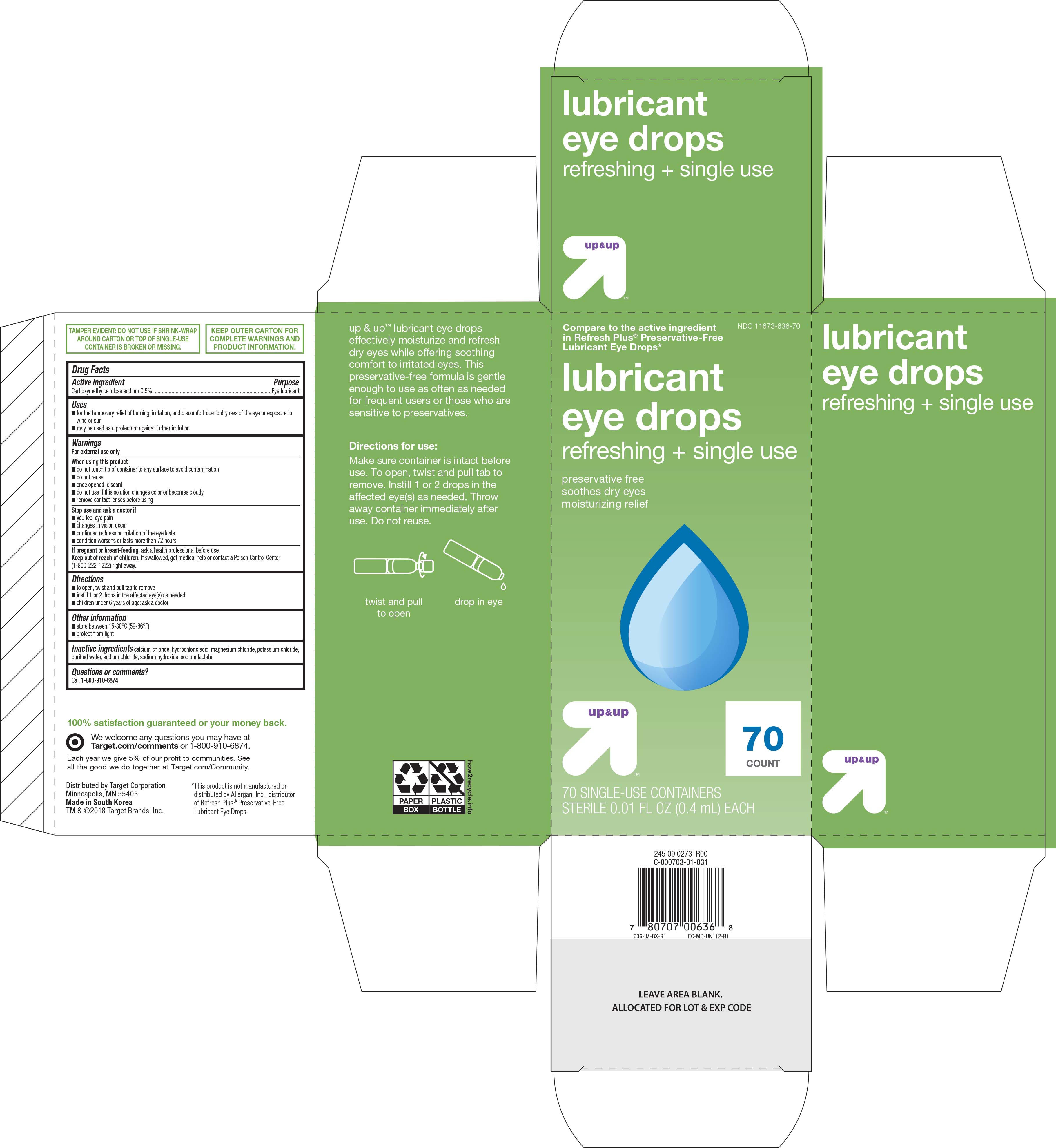 DRUG LABEL: Up and Up Lubricant Refreshing
NDC: 11673-636 | Form: SOLUTION/ DROPS
Manufacturer: Target Corporation
Category: otc | Type: HUMAN OTC DRUG LABEL
Date: 20180419

ACTIVE INGREDIENTS: CARBOXYMETHYLCELLULOSE SODIUM 5 mg/1 mL
INACTIVE INGREDIENTS: CALCIUM CHLORIDE; HYDROCHLORIC ACID; MAGNESIUM CHLORIDE; POTASSIUM CHLORIDE; SODIUM HYDROXIDE; SODIUM LACTATE; WATER

Up & Up Preservative Free Eye Drops 70 ct. NBE Refresh Plus 636 (2018)

Active ingredient Purpose

Carboxymethylcellulose sodium 0.5%..........................Eye lubricant

Uses

- for the temporary relief of burning, irritation, and discomfort due to dryness of the eye or exposure to wind or sun
- may be used as a protectant against further irritation

Warnings

For external use only

When using this product

- do not touch tip of container to any surface to avoid contamination
- do not reuse
- once opened, discard
- do not use if this solution changes color or becomes cloudy
- remove contact lenses before using

Stop use and ask a doctor if

- you feel eye pain
- changes in vision occur
- continued redness or irritation of the eye lasts
- condition worsens or lasts more than 72 hours

PREGNANCY OR BREAST FEEDING

If pregnant or breast-feeding, ask a health professional before use.

Keep out of reach of children. If swallowed, get medical help or contact a Poison Control Center (1-800-222-1222) right away.

Directions

- to open, twist and pull tab to remove
- instill 1 or 2 drops in the affected eye(s) as needed
- children under 6 years of age: ask a doctor

Other information

- store between 15-30°C (59-86°F)
- protect from light

INACTIVE INGREDIENT

Inactive ingredients calcium chloride, hydrochloric acid, magnesium chloride, potassium chloride, purified water, sodium chloride, sodium hydroxide, sodium lactate

DOSAGE AND ADMINISTRATION

Distributed by:

Target Corporation

Minneapolis, MN 55403

Made in South Korea